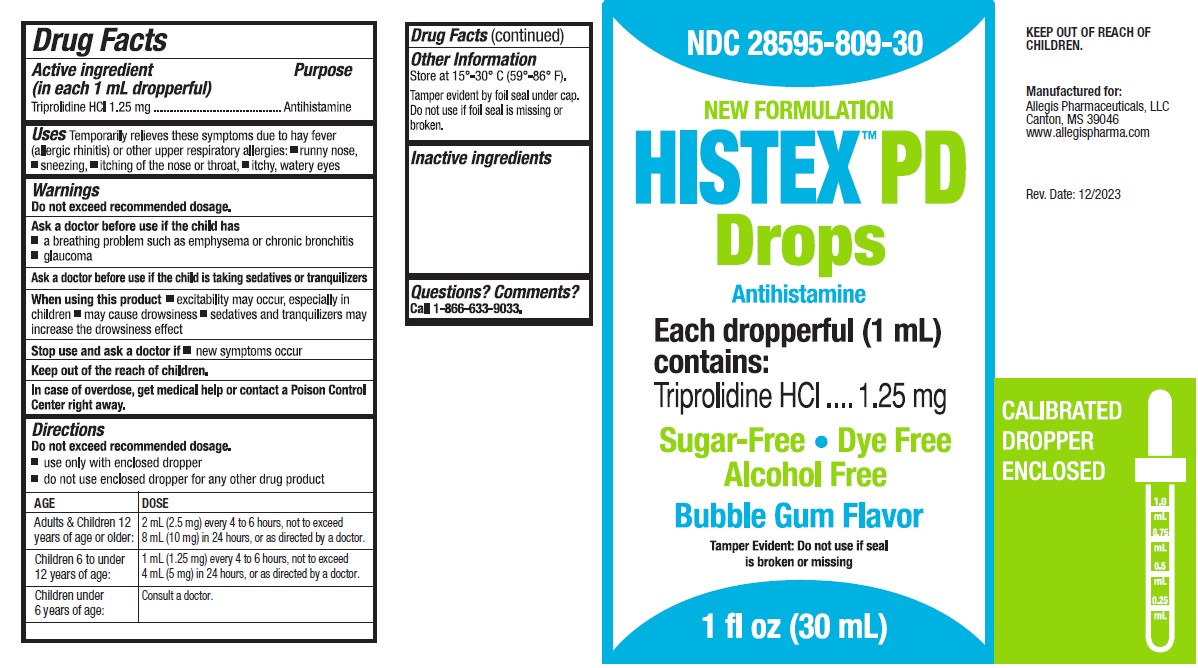 DRUG LABEL: HISTEX PD Drops New Formulation
NDC: 28595-809 | Form: SYRUP
Manufacturer: Allegis Pharmaceuticals, LLC
Category: otc | Type: HUMAN OTC DRUG LABEL
Date: 20250108

ACTIVE INGREDIENTS: TRIPROLIDINE HYDROCHLORIDE 1.25 mg/1 mL
INACTIVE INGREDIENTS: SUCRALOSE; SODIUM BENZOATE; CITRIC ACID MONOHYDRATE; GLYCERIN; PROPYLENE GLYCOL; WATER; SODIUM CITRATE, UNSPECIFIED FORM; SORBITOL

HISTEX™ PD New Formulation

Drug Facts

Active ingredient (in each 1 mL dropperful)

Triprolidine HCl 1.25 mg

Purpose

Antihistamine

Uses

temporarily relieves these symptoms due to hay fever (allergic rhinitis) or other upper respiratory allergies:

- runny nose
- sneezing
- itching of the nose or throat
- itchy, watery eyes

Warnings

Do not exceed recommended dosage.

Ask a doctor before use if the child has

- a breathing problem such as emphysema or chronic bronchitis
- glaucoma

Ask a doctor before use if the child is taking sedatives or tranquilizers

When using this product

- excitability may occur, especially in children
- may cause drowsiness
- sedatives and tranquilizers may increase the drowsiness effect

Stop use and ask a doctor if

- new symptoms occur

Keep out of the reach of children.

In case of overdose, get medical help or contact a Poison Control Center right away.

Directions

Do not exceed recommended dosage.

- use only the enclosed dropper.
- do not use enclosed dropper for any other drug products.

AGE | DOSE
Adutls & Children 12 years of age or older: | 2 mL (2.5 mg) every 4 to 6 hours, not to exceed 8 mL (10 mg) in 24 hours or as directed by a doctor.
Children 6 to under12 years of age: | 1 mL (1.25 mg) every 4 to 6 hours, not to exceed 4 mL (5 mg) in 24 hours or as directed by a doctor.
Children under 6 years of age: | Consult a docotor.

Other Information

Store at 15°-30° C (59°-86° F).

Tamper evident by foil seal under cap. Do not use if foil seal is missing or broken.

Inactive ingredients

bubble gum flavor, citric acid, glycerin, propylene glycol, purified water, sodium benzoate, sodium citrate, sorbitol solution, sucralose.

Questions? Comments?

Call 1-866-633-9033.

PRINCIPAL DISPLAY PANEL - 30 mL Bottle Carton

NDC 28595-809-30

HISTEX™ PD New Formulation
Drops

Antihistamine

Each dropperful (1 mL)
contains:
Triprolidine HCl
1.25 mg

Sugar-Free • Dye Free
Alcohol Free

Bubble Gum Flavor

1 fl oz (30 mL) Bottle